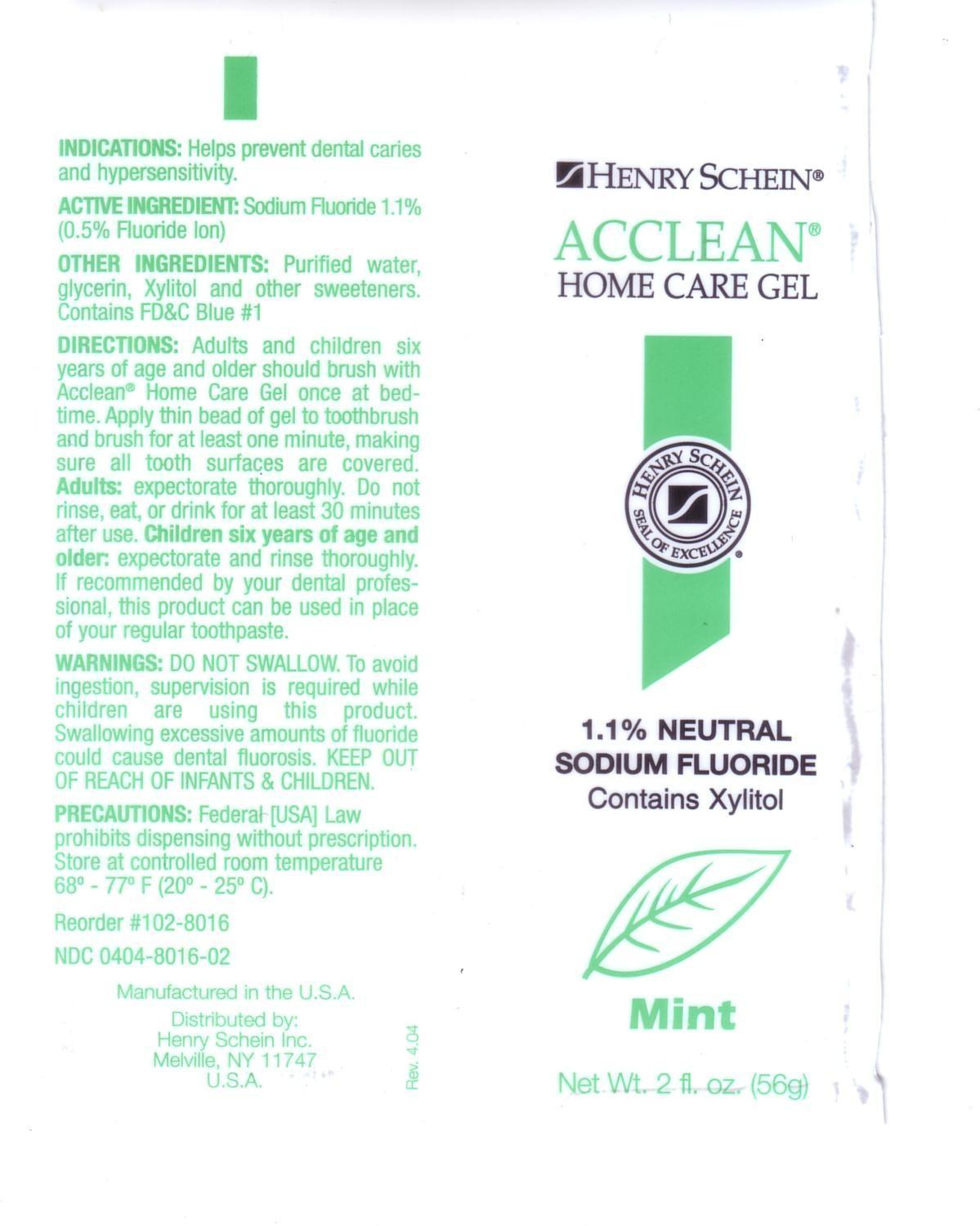 DRUG LABEL: Acclean
                
NDC: 0404-8016 | Form: GEL, DENTIFRICE
Manufacturer: Henry Schein Inc.
Category: prescription | Type: HUMAN PRESCRIPTION DRUG LABEL
Date: 20130727

ACTIVE INGREDIENTS: SODIUM FLUORIDE 5 mg/1 g
INACTIVE INGREDIENTS: WATER; GLYCERIN; XYLITOL; FD&C BLUE NO. 1

Drug Facts

INACTIVE INGREDIENT

Other Ingredients - Purified water, glycerin, Xylitol and other sweeteners, Contains F D and C Blue No. 1

Active Ingredient: Sodium Fluoride 1.1%

(0.5% Fluoride Ion)

Indications: Helps prevent dental caries and hypersensitivity

DOSAGE AND ADMINISTRATION

Directions: Adults and children six years of age and older should brush with

Acclean Home Care Gel once at bedtime. Apply thin bead of gel to toothbrush

and brush for at least one minute, making sure all tooth surfaces are covered.

Adults: expectorate thoroughly. Do not rinse, eat, or drink for at least 30 minutes

after use. Children six years of age and older: expectorate and rinse thoroughly.

If recommended by your dentist professional, this product can be used in place

of your regular toothpaste.

WARNINGS: DO NOT SWALLOW. To avoid ingestion,

supervision is required while children are using this product.

Swallowing excessive amounts of fluoride could cause dental fluorosis.

KEEP OUT OF REACH OF INFANTS AND CHILDREN.

Enter section text here PRECAUTIONS: Federal (USA) Law

prohibits dispensing without prescription. Store at controlled

room temperature 68 - 77 F (20 - 25 C).